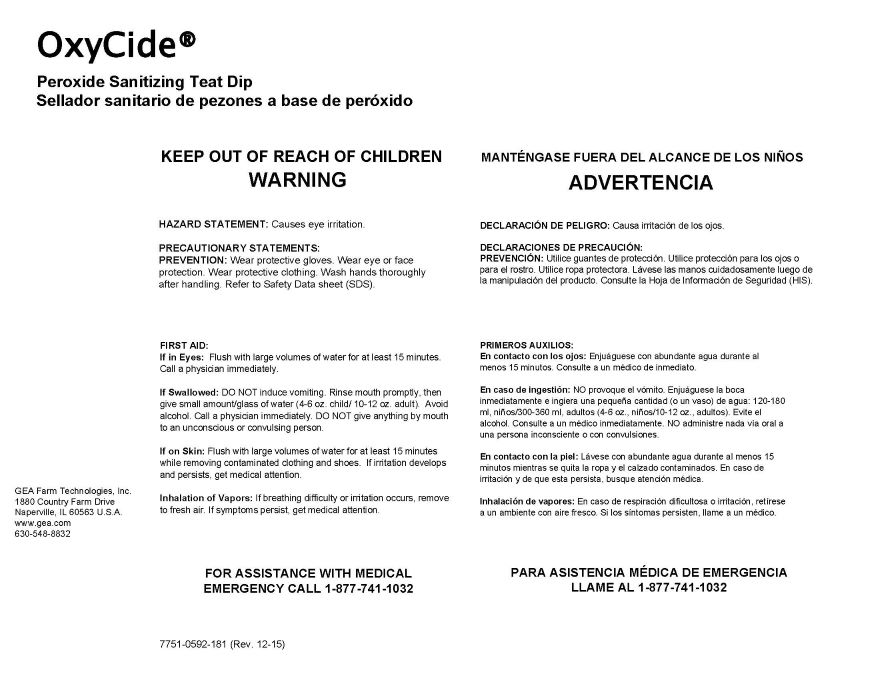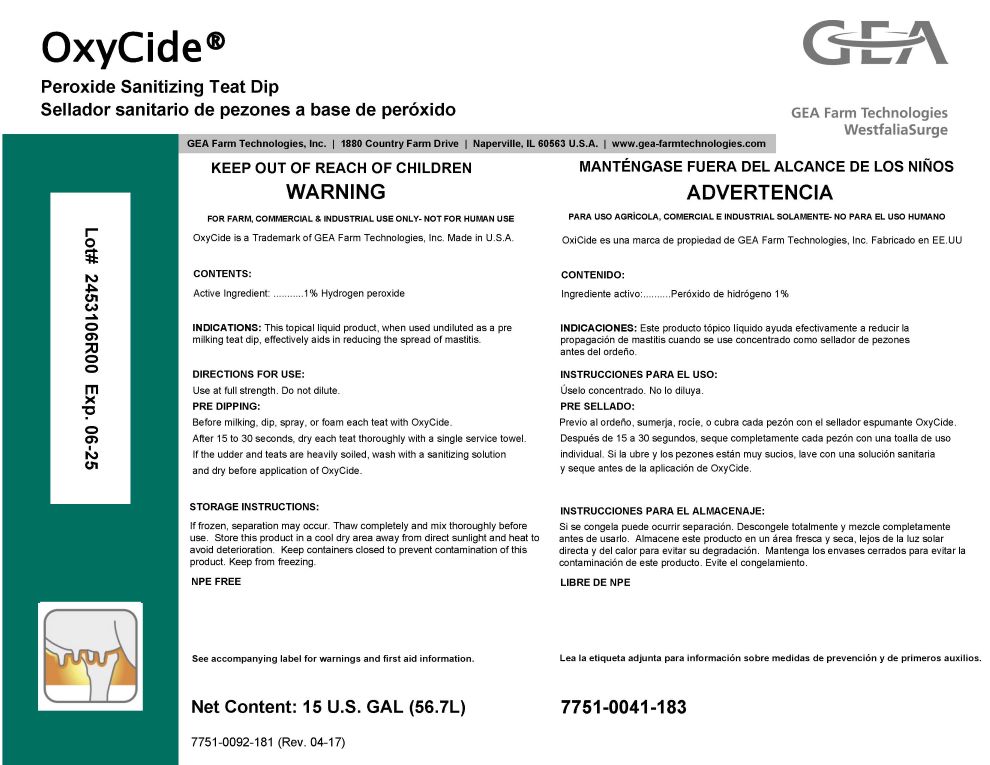 DRUG LABEL: GEA OxyCide
NDC: 51070-7006 | Form: LIQUID
Manufacturer: GEA Farm Technologies, Inc.
Category: animal | Type: OTC ANIMAL DRUG LABEL
Date: 20240606

ACTIVE INGREDIENTS: HYDROGEN PEROXIDE 1 g/100 g
INACTIVE INGREDIENTS: GLYCERIN; CITRIC ACID MONOHYDRATE; C12-16 ALCOHOLS; UREA; ASCORBIC ACID; LAURAMINE OXIDE; FD&C YELLOW NO. 5

OxyCide

ACTIVE INGREDIENT

CONTENTS:

Active Ingredient: 1% Hydrogen peroxide

Net Content: 15 U.S. GAL (56.7L)

KEEP OUT OF REACH OF CHILDREN

WARNING

PRECAUTIONS

HAZARD STATEMENT: Causes eye irritation.

PRECAUTIONARY STATEMENTS:

PREVENTION: Wear protective gloves. Wear eye or face protection. Wear protective clothing. Wash hands thoroughly after handling. Refer to Safety Data sheet (SDS).

USER SAFETY WARNINGS

FIRST AID:

If in Eyes: Flush with large volumes of water for at least 15 minutes. Call a physician immediately.
If Swallowed: DO NOT induce vomiting. Rinse mouth promptly, then give small amount/glass of water (4-6 oz. child / 10-12 oz. adult). Avoid alcohol. Call a physician immediately. DO NOT give anything by mouth to an unconscious or convulsing person.
If on Skin: Flush with large volumes of water for at least 15 minutes while removing contaminated clothing and shoes. If irritation develops and persists, get medical attention.
Inhalation of Vapors: If breathing difficulty or irritation occurs, remove to fresh air. If symptoms persist, get medical attention.

FOR ASSISTANCE WITH MEDICAL EMERGENCY

CALL 1-877-741-1032

FOR FARM, COMMERCIAL & INDUSTRIAL USE ONLY- NOT FOR HUMAN USE

OxyCide is a Trademark of GEA Farm Technologies, Inc. Made in U.S.A.

INDICATIONS AND USAGE

INDICATIONS: This topical liquid product, when used undiluted as a pre milking teat dip, effectively aids in reducing the spread of mastitis.

DOSAGE AND ADMINISTRATION

DIRECTIONS FOR USE: Use at full strength. Do not dilute.

PRE DIPPING: Before milking, dip, spray, or foam each teat with OxyCide. After 15 to 30 seconds, dry each treat thoroughly with a single service towel. If the udder and teats are heavily soiled, wash with a sanitizing solution and dry before application of OxyCide.

STORAGE INSTRUCTIONS:

If frozen, separation may occur. Thaw completely and mix thoroughly before use. Store this product in a cool dry area away from direct sunlight and heat to avoid deterioration. Keep containers closed to prevent contamination of this product. Keep from freezing.

NPE FREE

See accompanying label for warnings and first aid information.

7751-0092-181 (Rev. 04-17)

GEA Farm Technologies, Inc. • 1880 Country Farm Drive • Naperville, IL 60563 U.S.A • www.gea-farmtechnologies.com

7751-0041-183

GEA Farm Technologies, Inc.

1880 Country Farm Dr.

Naperville, IL 60563 U.S.A.

www.gea.com

630-548-8832

7751-0592-181 (Rev. 12-15)

PACKAGE LABEL

OxyCide®

Peroxide Sanitizing Teat Dip